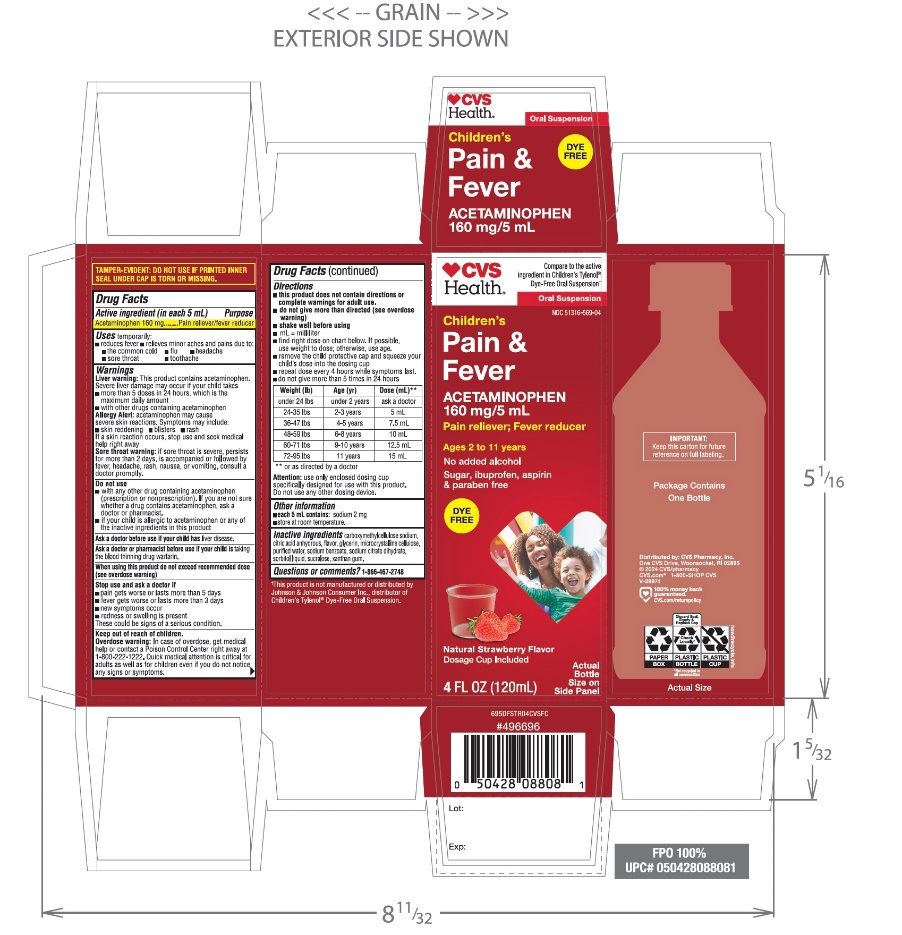 DRUG LABEL: Childrens Pain plus Fever Relief
NDC: 51316-569 | Form: SUSPENSION
Manufacturer: CVS PHARMACY
Category: otc | Type: HUMAN OTC DRUG LABEL
Date: 20251209

ACTIVE INGREDIENTS: ACETAMINOPHEN 160 mg/5 mL
INACTIVE INGREDIENTS: CARBOXYMETHYLCELLULOSE SODIUM, UNSPECIFIED; ANHYDROUS CITRIC ACID; GLYCERIN; MICROCRYSTALLINE CELLULOSE; WATER; SODIUM BENZOATE; TRISODIUM CITRATE DIHYDRATE; SORBITOL SOLUTION; SUCRALOSE; XANTHAN GUM

Children’s Pain + Fever Relief

Drug Facts

Active ingredient (in each 5 mL)

Acetaminophen 160 mg

Purpose

Pain reliever/fever reducer

Uses

- temporarily:
- reduces fever
- relieves minor aches and pains due to:
  - the common cold
  - flu
  - headache
  - sore throat
  - toothache

Warnings

Liver warning

This product contains acetaminophen. Severe liver damage may occur if your child takes

- more than 5 doses in 24 hours, which is the maximum daily amount
- with other drugs containing acetaminophen

- Allergy alert:acetaminophen may cause severe skin reactions. Symptoms may include:

- skin reddening
- blisters
- rash

If a skin reaction occurs, stop use and seek medical help right away.

Sore throat warning:if sore throat is severe, persists for more than 2 days, is accompanied, or followed by fever, headache, rash, nausea, or vomiting, consult a doctor promptly.

Do not use

- with any other drug containing acetaminophen (prescription or nonprescription). If you are not sure whether a drug contains acetaminophen, ask a doctor or pharmacist.
- if your child is allergic to acetaminophen or any of the inactive ingredients in this product

Ask a doctor before use if your child hasliver disease

Ask a doctor or pharmacist before use if your child istaking the blood thinning drug warfarin.

When using this product do not exceed recommended dose (see overdose warning)

Stop use and ask a doctor if

- pain gets worse or lasts more than 5 days
- fever gets worse or lasts more than 3 days
- new symptoms occur
- redness or swelling is present

These could be signs of a serious condition.

Keep out of reach of children.

Overdose warning

In case of overdose, get medical help or contact a Poison Control Center right away. (1-800-222-1222) Quick medical attention is critical for adults as well as for children even if you do not notice any signs or symptoms.

Directions

- this product does not contain directions or complete warnings for adult use.
- do not give more than directed (see overdose warning)
- shake well before using
- mL = milliliter
- find right dose on chart below. If possible, use weight to dose; otherwise, use age.
- remove the child protective cap and squeeze your child's dose into the dosing cup
- repeat dose every 4 hours while symptoms last
- do not give more than 5 times in 24 hours

Weight (lb) | Age (yr) | Dose (mL) **
under 24 | under 2 years | ask a doctor
24-35 | 2-3 years | 5 mL
36-47 | 4-5 years | 7.5 mL
48-59 | 6-8 years | 10 mL
60-71 | 9-10 years | 12.5 mL
72-95 | 11 years | 15 mL

Attention:use only enclosed dosing cup specifically designed for use with this product. Do not use any other dosing device.

Other information

- each 5 mL contains: sodium 2 mg
- store at room temperature

Inactive ingredients

carboxymethylcellulose sodium, anhydrous citric acid, flavors, glycerin, microcrystalline cellulose, purified water, sodium benzoate, sodium citrate dihydrate, sorbitol solution, sucralose, xanthan gum

Questions or comments?

1-866-467-2748

PRINCIPAL DISPLAY PANEL

Compare to the active ingredient in Children’s Tylenol® Dye-Free Oral Suspension*

NDC 51316-569-04

Children’s

Pain+Fever Relief

Acetaminophen
Oral Suspension

Pain Reliever-Fever Reducer

1. No Added Alcohol
2. Sugar Free
3. Dye Free
4. Aspirin Free
5. Ibuprofen Free
6. No Parabens

Ages 2-11 Years
Natural Strawberry Flavor

4 FL. OZ. (120 mL)
160 mg per 5 mL

*This product is not manufactured or distributed by Johnson & Johnson Consumer Inc., the distributor of Children’s Tylenol® Dye-Free Oral Suspension.

Distributed by: